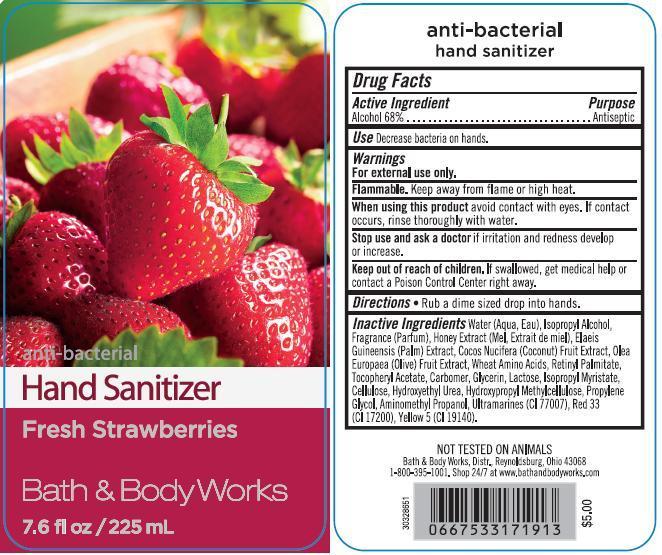 DRUG LABEL: Anti-Bacterial Hand Sanitizer
NDC: 62670-4600 | Form: GEL
Manufacturer: Bath & Body Works, Inc.
Category: otc | Type: HUMAN OTC DRUG LABEL
Date: 20130726

ACTIVE INGREDIENTS: ALCOHOL 68 mL/100 mL
INACTIVE INGREDIENTS: WATER

ACTIVE INGREDIENT

Alcohol 68%

PURPOSE

Antiseptic

USE

Decrease bacteria on hands.

WARNINGS

For external use only.

FLAMMABLE

Keep away from flame or high heat.

WHEN USING THIS PRODUCT

avoid contact with eyes. If contact occurs, rinse thoroughly with water.

STOP USE AND ASK A DOCTOR

if irritation and redness develop or increase.

KEEP OUT OF REACH OF CHILDREN

If swallowed, get medical help or contact a Poison Control Center right away.

DIRECTIONS

- Rub a dime sized drop into hands.

INACTIVE INGREDIENTS

Water (Aqua, Eau), Isopropyl Alcohol, Fragrance (Parfum), Honey Extract (Mel, Extrait de miel), Elaeis Guineensis (Palm) Extract, Cocos Nucifera (Coconut) Fruit Extract, Olea Europaea (Olive) Fruit Extract, Wheat Amino Acids, Retinyl Palmitate, Tocopheryl Acetate, Carbomer, Glycerin, Lactose, Isopropyl Myristate, Cellulose, Hydroxyethyl Urea, Hydroxypropyl Methylcellulose, Propylene Glycol, Aminomethyl Propanol, Ultramarines (CI 77007), Red 33 (CI 17200), Yellow 5 (CI 19140).

COMPANY INFORMATION

Bath & Body Works, Distr.

Reynoldsburg, Ohio 43068

1-800-395-1001

www.bathandbodyworks.com